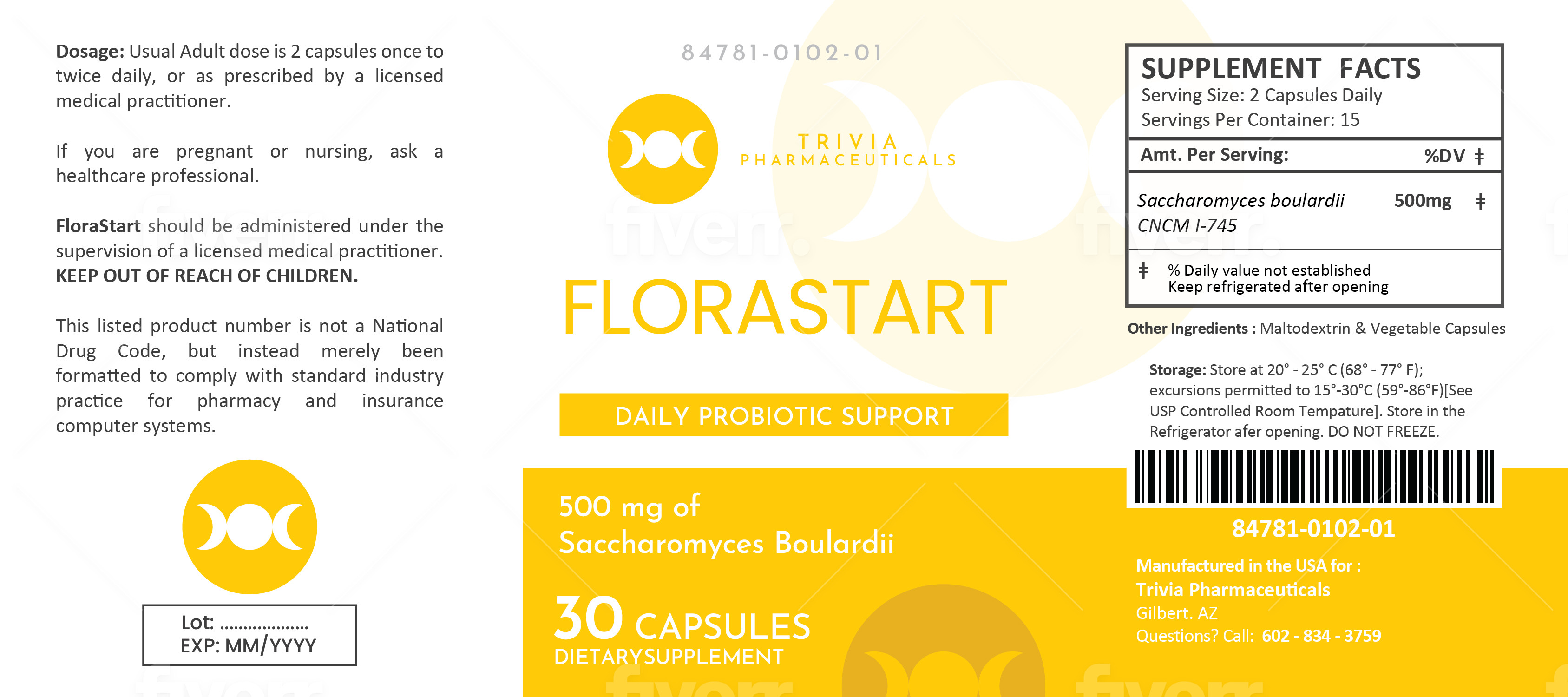 DRUG LABEL: FLORASTART
NDC: 84781-102 | Form: CAPSULE
Manufacturer: Trivia Pharmaceuticals, LLC
Category: other | Type: DIETARY SUPPLEMENT
Date: 20250205

ACTIVE INGREDIENTS: SACCHAROMYCES CEREVISIAE VAR. BOULARDII CNCM I-1079 250 mg/1 1
INACTIVE INGREDIENTS: MALTODEXTRIN

Florastart Probiotic Capsules
Dietary Supplement

HEALTH CLAIM:

Florastart Capsules

Dietary Supplement

Dispensed by Prescription

Supplement Facts

Serving Size: 2 Capsules Daily

Servings Per Container: 15

Amount Per Serving:

% Daily Value

Saccharomyces Boulardii

500 mg **

** Daily values not established

Other Ingredients: Maltodextrin, Vegetable Capsules

DESCRIPTION:

Florastart is an orally administered prescription probiotic formulation for the clinical dietary management of suboptimal nutritional status in patients where advanced supplementation is required and nutritional supplementation in physiologically stressful conditions for maintenance of good health is needed.

Florastart should be administered under the supervision of a licensed medical practitioner.

This listed product is not a National Drug Code, but instead has merely been formatted to comply with standard industry practice for pharmacy and insurance computer systems.

WARNINGS AND PRECAUTIONS:

This product is contraindicated in patients with a known hypersensitivity to any of the ingredients.

Florastart should only be used under the direction and supervision of a licensed medical practitioner. Use with caution in patients that may have a medical condition, are pregnant, lactating, trying to conceive, under the age of 18, or taking medications.

DOSAGE AND ADMINISTRATION:

Usual adult dose is 2 capsules by mouth daily once or twice daily, or as prescribed by a licensed medical practitioner.

HOW SUPPLIED:

Florastart is supplied as clear capsules dispensed in plastic bottles of 30 ct.

84781-102-01

Reserved for Professional Recommendation

All prescriptions using this product shall be pursuant to state statutes as applicable. This is not an Orange Book product. This product may be administered only under a physician’s supervision. There are no implied or explicit claims on therapeutic equivalence.

Manufactured for:
Trivia Pharmaceuticals

Gilbert, AZ

STORAGE:

Handling (before opening):
Product is sensitive to moisture and heat. Keep bottle tightly closed in a dry, cool place. Store at 20^0C to 25^0C (68^0F to 77^0F).

Handling (after opening):
Store in the refrigerator after opening, DO NOT FREEZE. Store at 2^0C to 8^0C (35^0F to 46^0F).

Call your doctor about side effects. You may report side effects to FDA at 1-800-FDA-1088.